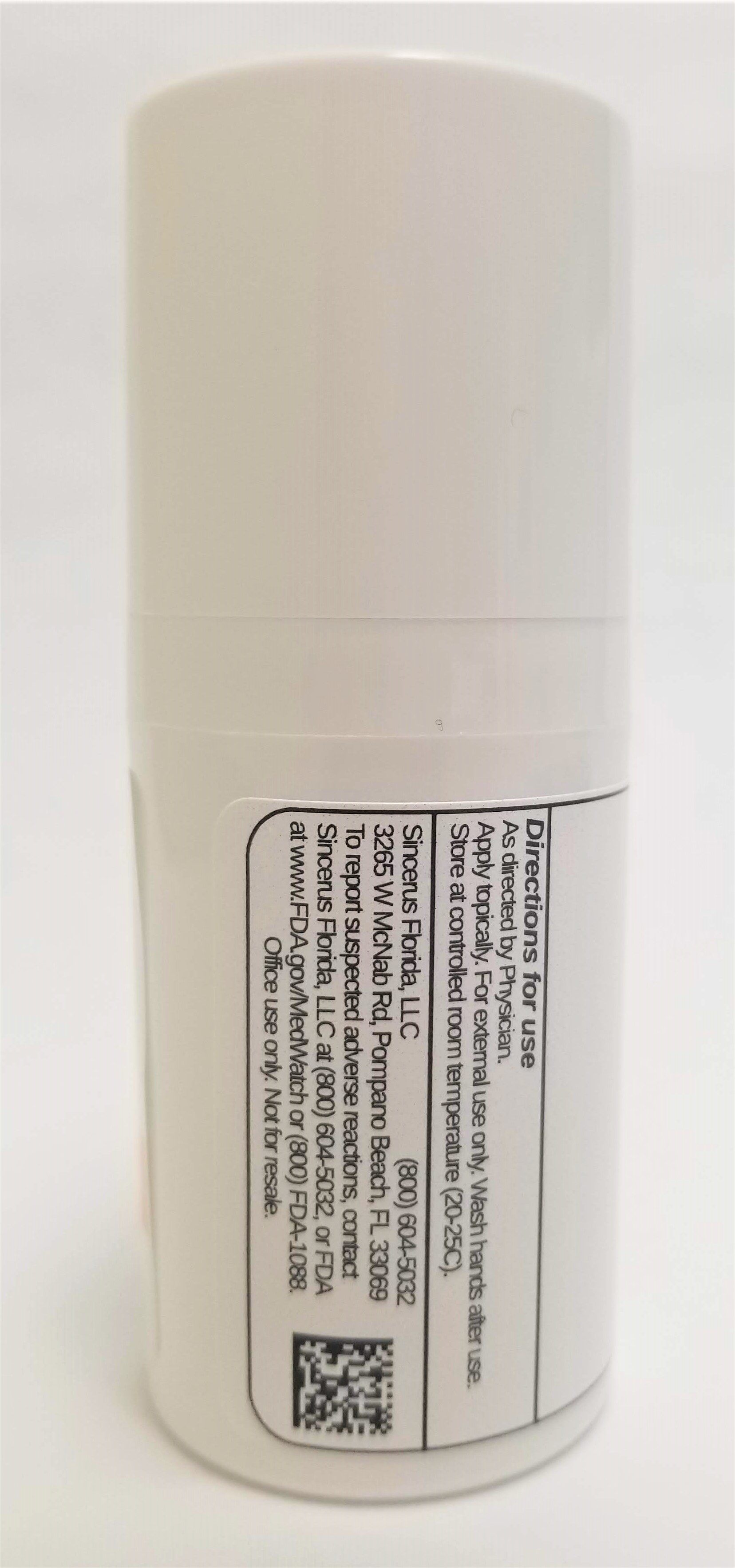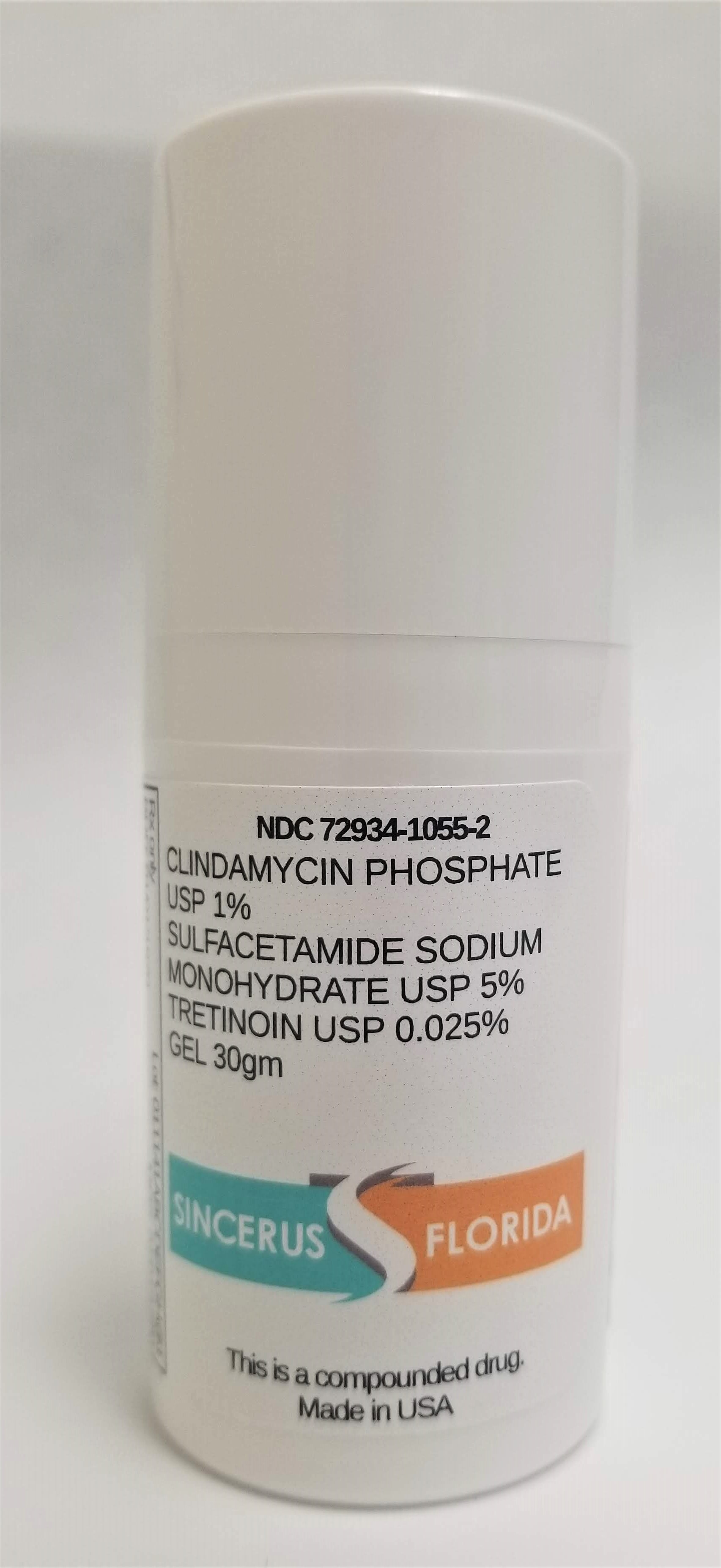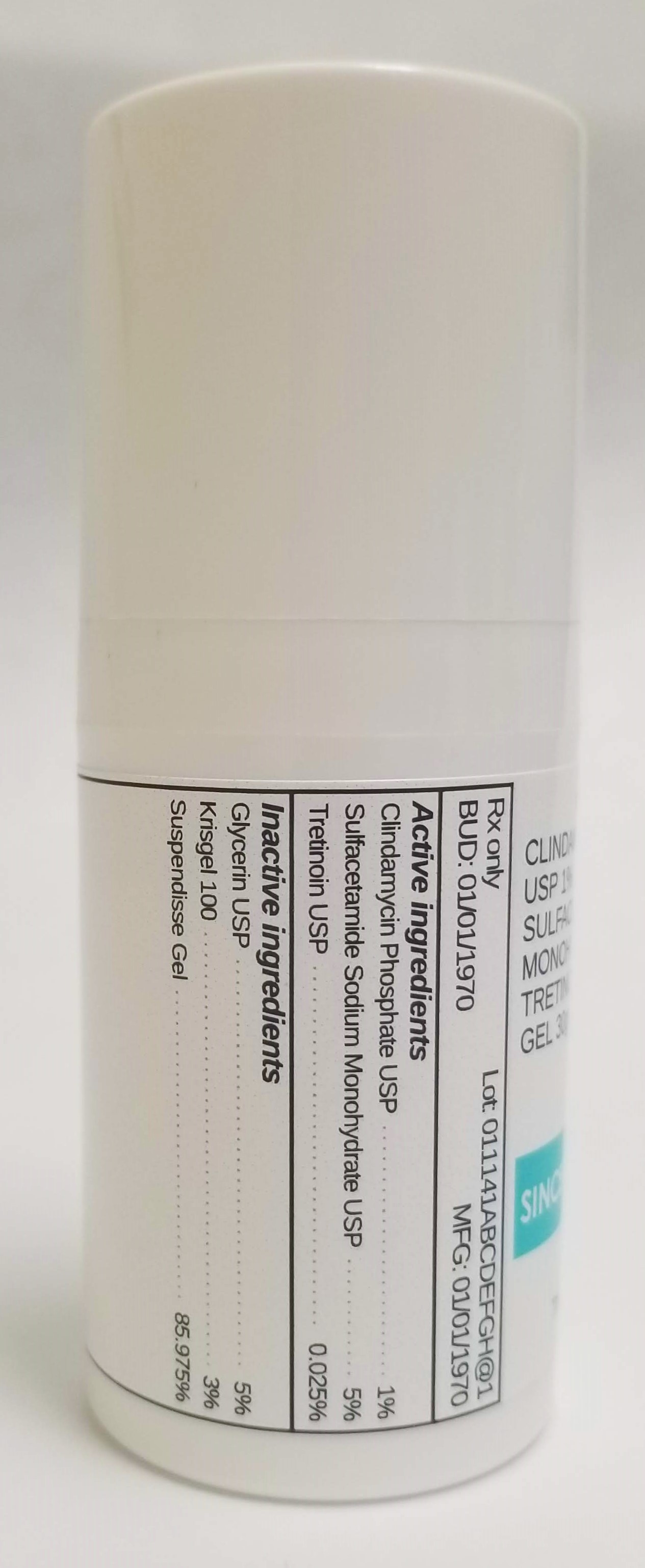 DRUG LABEL: CLINDAMYCIN 1% / SODIUM SULFACETAMIDE MONOHYDRATE 5% / TRETINOIN 0.025%
NDC: 72934-1055 | Form: GEL
Manufacturer: Sincerus Florida, LLC
Category: prescription | Type: HUMAN PRESCRIPTION DRUG LABEL
Date: 20190503

ACTIVE INGREDIENTS: CLINDAMYCIN PHOSPHATE 1 g/100 g; SULFACETAMIDE SODIUM 5 g/100 g; TRETINOIN 0.025 g/100 g

CLINDAMYCIN 1% / SODIUM SULFACETAMIDE MONOHYDRATE 5% / TRETINOIN 0.025%